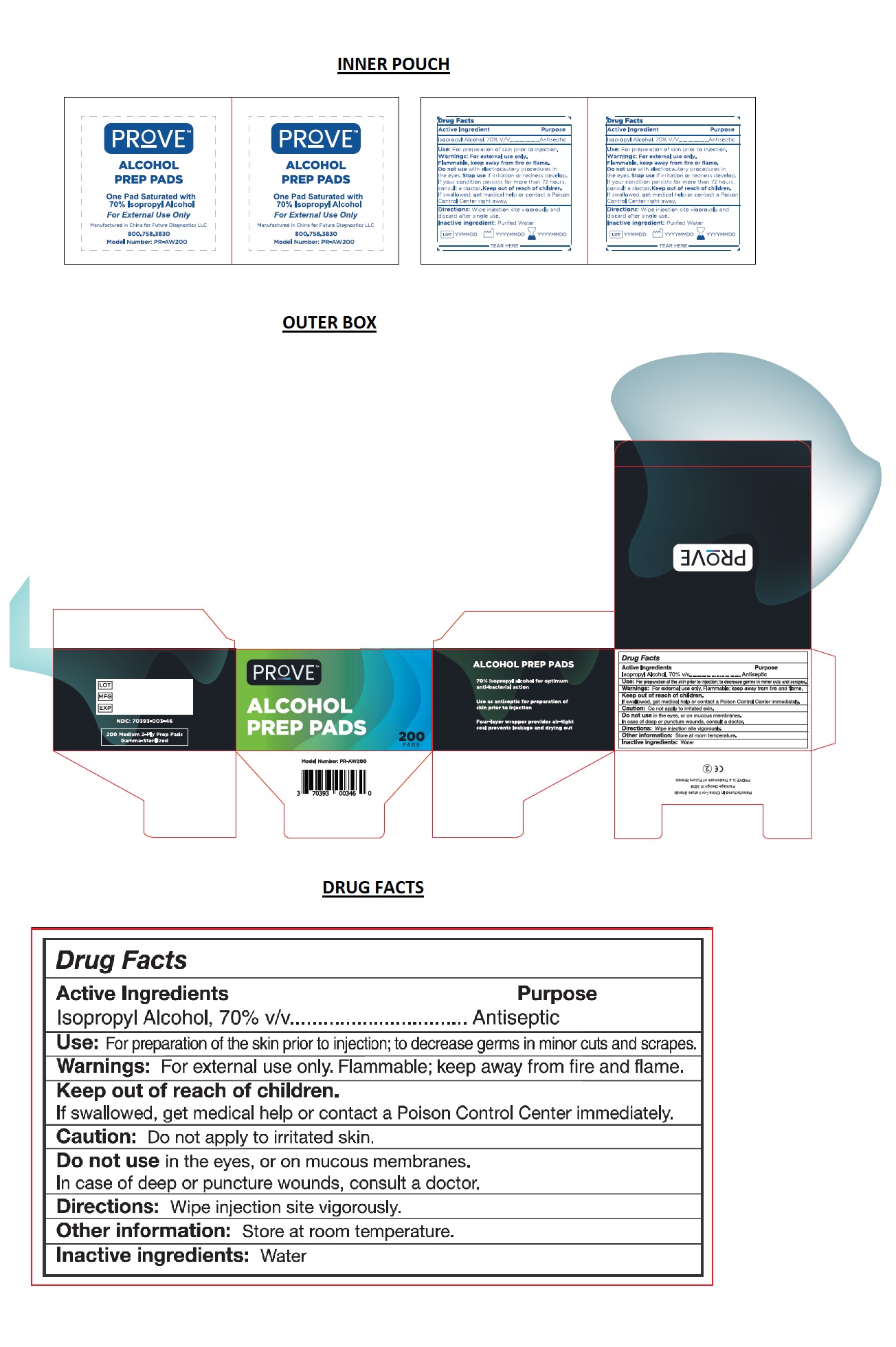 DRUG LABEL: PROVE ALCOHOL PREP PADS
NDC: 70393-003 | Form: SWAB
Manufacturer: Future Diagnostics Llc
Category: otc | Type: HUMAN OTC DRUG LABEL
Date: 20200330

ACTIVE INGREDIENTS: ISOPROPYL ALCOHOL 0.7 mL/1 1
INACTIVE INGREDIENTS: WATER

PROVETM ALCOHOL PREP PADS

Active Ingredients

Isopropyl Alcohol, 70% v/v

Purpose

Antiseptic

INDICATIONS AND USAGE

Use: For preparation of the skin prior to injection: to decrease germs in minor cuts and scrapes.

WARNINGS

Warnings: For external use only. Flammable; keep away from the ﬁre and ﬂame.

Caution: Do not apply to irritated skin.

Do not use in the eyes or on mucous membranes.

In case of deep or puncture wounds, consult a doctor.

Keep out of reach of children.

If swallowed, get medical help or contact a Poison Control Center immediately.

DOSAGE AND ADMINISTRATION

Directions: Wipe injection site vigorously.

Other information: Store at room temperature.

Inactive ingredients: Water

70% Isopropyl alcohol for optimum anti-bacterial action

Use as antiseptic for preparation of skin prior to injection

Four-layer wrapper provides air-tight seal prevents leakage and drying out

Manufactured In China For Future Brands

PROVE is a Trademark of Future Brands